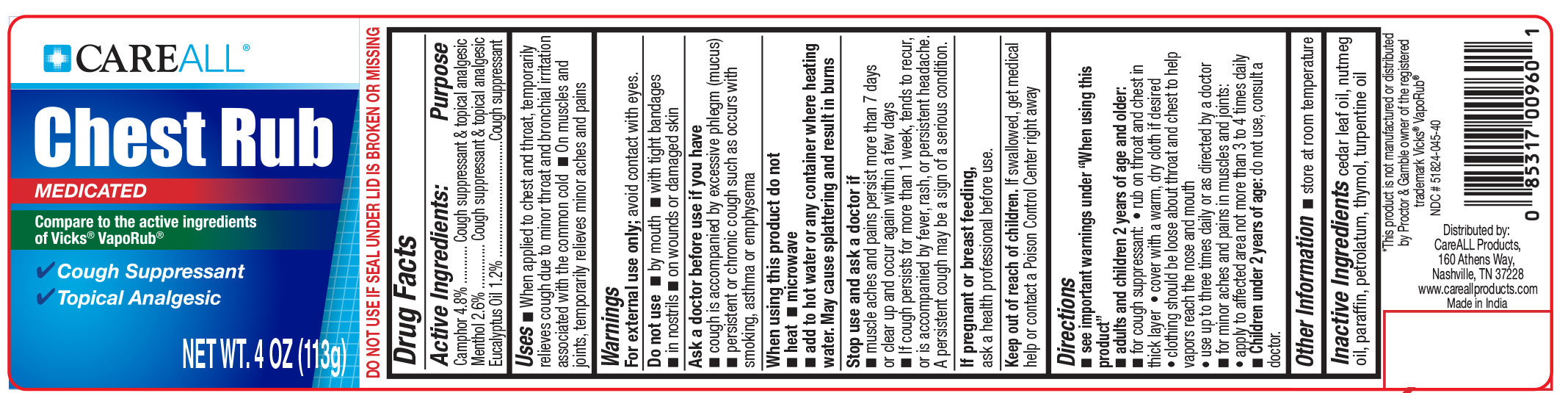 DRUG LABEL: CareAll Medicated Chest Rub
NDC: 51824-045 | Form: OINTMENT
Manufacturer: New World Imports, Inc
Category: otc | Type: HUMAN OTC DRUG LABEL
Date: 20251201

ACTIVE INGREDIENTS: CAMPHOR (SYNTHETIC) 0.048 g/1 g; MENTHOL 0.026 g/1 g; EUCALYPTUS OIL 0.012 g/1 g
INACTIVE INGREDIENTS: CEDAR LEAF OIL; NUTMEG OIL; PARAFFIN; PETROLATUM; THYMOL; TURPENTINE OIL

ACTIVE INGREDIENT

Camphor 4.8%

Menthol 2.6%

Eucalyptus oil 1.2%

PURPOSE

Camphor: cough suppressant / topical analgesic

Menthol: cough suppressant / topical analgesic

Eucalyptus oil: cough suppressant

Keep out of reach of children. If swallowed, get medical help or contact a Poison Control Center right away

INDICATIONS AND USAGE

- When applied to chest and throat, temporarily relieves cough due to minor throat and bronchial irritations associated with the common cold
- On muscles and joints, temporarily relieves minor aches and pains

WARNINGS

For external use only. Avoid contact with eyes.

Do not use

- by mouth
- in nostrils
- on wounds or damaged skin
- with tight bandages

Ask a doctor before use if you have

- cough is accompanied by excessive phlegm (mucus)
- persistent or chronic cough such as occurs with smoking, asthma or emphysema

When using this product do not

- heat
- microwave
- add to hot water or any container where heating water. May cause splattering and result in burns

Stop use and ask a doctor if

- muscle aches/pain persist more than 7 days or clear up and occur again within a few days
- cough lasts more than 1 week, tends to recur, or is accompanied by fever, rash, or persistent headache. A persistent cough may be a sign of a serious condition.

If pregnant or breast feeding,ask a health professional before use

DOSAGE AND ADMINISTRATION

See important warnings under "When using this product"

- Adults and children 2 years of age and older:
- for cough suppressent:
- rub on throat and chest in thick layer
- cover with a warm, dry cloth if desired
- clothing shoudl be loose about throat and chest to help vapors reach the nose and mouth
- use up to three times daily or as directed by doctor
- for minor ache and pains in muscle and joints:
- apply to affecteed area not more than 3 to 4 times daily
- Children under 2 years of age:do not use, consult a doctor

OTHER SAFETY INFORMATION

Store at room temperature

INACTIVE INGREDIENT

cedar leaf oil, nutmeg oil, paraffin, petrolatum, thymol, turpentine oil